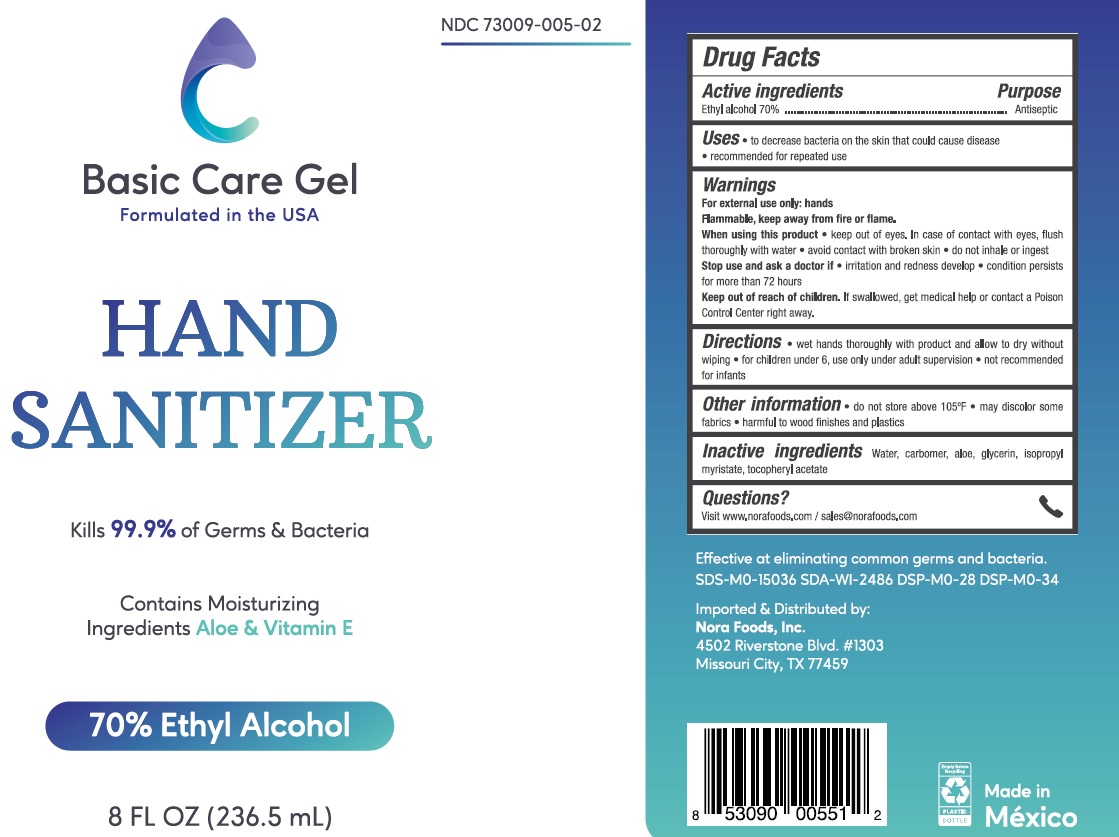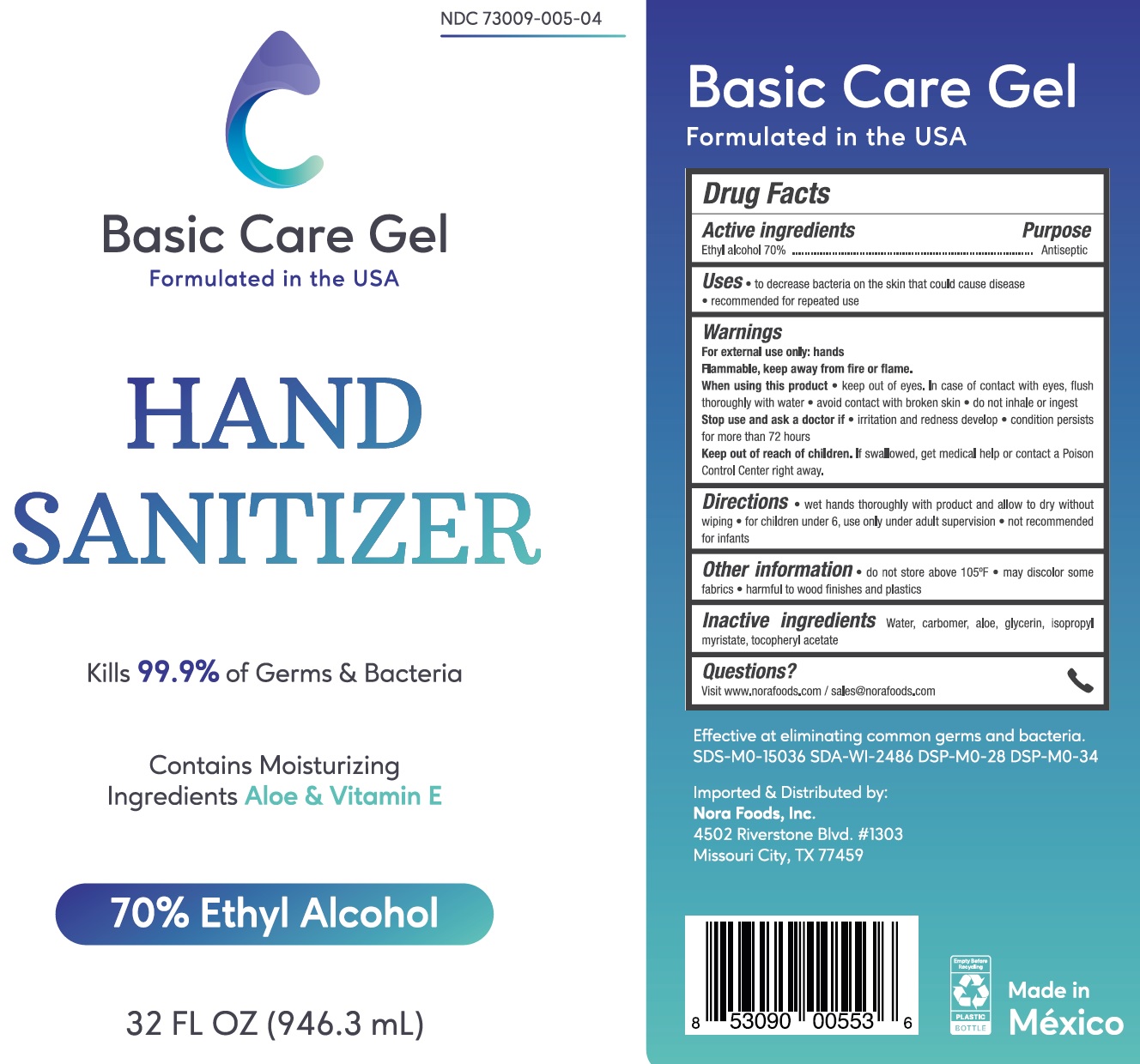 DRUG LABEL: Basic Care
NDC: 79695-015 | Form: GEL
Manufacturer: Adco Trading Inc
Category: otc | Type: HUMAN OTC DRUG LABEL
Date: 20200721

ACTIVE INGREDIENTS: ALCOHOL 0.7 mL/1 mL
INACTIVE INGREDIENTS: WATER; CARBOMER HOMOPOLYMER, UNSPECIFIED TYPE; ALOE; GLYCERIN; ISOPROPYL MYRISTATE; .ALPHA.-TOCOPHEROL ACETATE

Basic Care Gel

Active ingredients

Ethyl alcohol 70%

Purpose

Antiseptic

Uses

- to decrease bacteria on the skin that could cause disease
- recommended for repeated use

Warnings

For external use only: hands

Flammable, keep away from fire or flame.

When using this product

- keep out of eyes. In case of contact with eyes, flush thoroughly with water
- avoid contact with broken skin
- do not inhale or ingest

Stop use and ask a doctor if

- irritation and redness develop
- condition persists for more than 72 hours

Keep out of reach of children.

If swallowed, get medical help or contact a Poison Control Center right away.

Directions

- wet hands thoroughly with product and allow to dry without wiping
- for children under 6, use only under adult supervision
- not recommended for infants

Other information

- do not store above 105°F
- may discolor some fabrics
- harmful to wood finishes and plastics

Inactive ingredients

Water, carbomer, aloe, glycerin, isopropyl myristate, tocopheryl acetate

Questions?

Visit www.norafoods.com / sales@norafoods.com